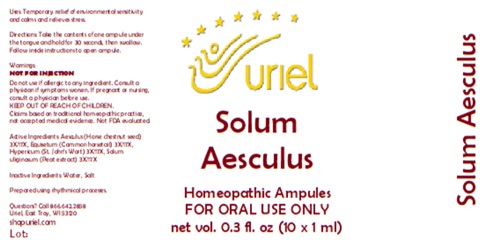 DRUG LABEL: Solum Aesculus
NDC: 48951-8193 | Form: LIQUID
Manufacturer: Uriel Pharmacy Inc.
Category: homeopathic | Type: HUMAN OTC DRUG LABEL
Date: 20251126

ACTIVE INGREDIENTS: HORSE CHESTNUT 3 [hp_X]/1 mL; EQUISETUM ARVENSE TOP 3 [hp_X]/1 mL; ST. JOHN'S WORT 3 [hp_X]/1 mL; SPHAGNUM SQUARROSUM PEAT 3 [hp_X]/1 mL
INACTIVE INGREDIENTS: SODIUM CHLORIDE; WATER

Solum Aesculus

PURPOSE

Uses: Temporary relief of environmental sensitivity and calms and relieves stress.

INDICATIONS AND USAGE

FOR ORAL USE ONLY

DOSAGE AND ADMINISTRATION

Directions: Take the contents of one ampule under the tongue and hold for 30 seconds, then swallow. Follow inside instructions to open ampule.

Warnings:
NOT FOR INJECTION
Do not use if allergic to any ingredient. Consult a physician if symptoms worsen. If pregnant or nursing, consult a physician before use.
Claims based on traditional homeopathic practice, not accepted medical evidence. Not FDA evaluated

KEEP OUT OF REACH OF CHILDREN.

ACTIVE INGREDIENT

Active Ingredients: Aesculus (Horse chestnut seed) 3X/17X, Equisetum (Common horsetail) 3X/17X, Hypericum (St. John’s Wort) 3X/17X, Solum uliginosum (Peat extract) 3X/17X

Inactive Ingredients: Water, Salt

Prepared using rhythmical processes.

Questions? Call 866.642.2858
Uriel, East Troy, WI 53120
shopuriel.com Lot: